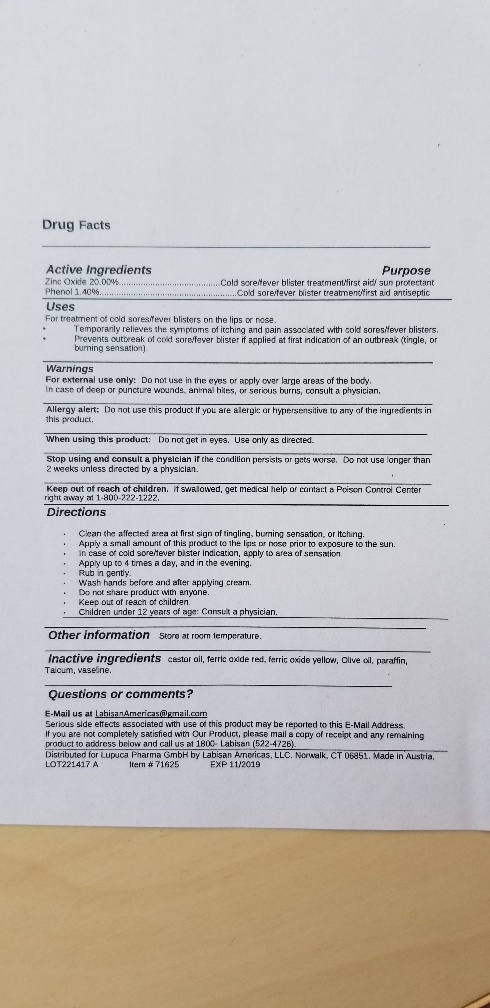 DRUG LABEL: Labisan
NDC: 72892-932 | Form: OINTMENT
Manufacturer: Labisan Americas, LLC.
Category: otc | Type: HUMAN OTC DRUG LABEL
Date: 20200606

ACTIVE INGREDIENTS: PHENOL 1.4 mg/100 mg; ZINC OXIDE 20 mg/100 mg
INACTIVE INGREDIENTS: OLIVE OIL; SHEA BUTTER; FERRIC OXIDE RED; CASTOR OIL; PARAFFIN; FERRIC OXIDE YELLOW

Zinc Oxide 20% part347 (suncreen) and 1.4% Phenol (Astringent) (part 310.545(a)(18)(ii).10b, #7- Phenol 0.5 - 1.5% within Monograph,Title 21 active ingredients..

Active ingredients

_________________________________________________________________

Active Ingredients Purpose

Zinc Oxide 20.00%................................................................Cold sore/fever blister treatment/first aid/ sun protectant

Phenol 4.00%........................................................................Cold sore/fever blister treatment/first aid antiseptic

Sulfur Praecipitotum 10.00%.................................................Cold sore/fever blister treatment/first aid antiseptic

___________________________________________________________________________________________

Inactive Ingredients

nactive ingredients Talcum, vaseline, shea butter, paraffin, Olive oil, castor oil, iron oxide yellow and red (for color).

___________________________

Keep out of reach Children

Keep out of reach of children. If swallowed, get medical help or contact a Poison Control Center right away at 1-800-222-1222.

______________

Warnings

For external use only: Do not use in the eyes, or apply over large areas of the body.

In case of deep or puncture wounds, animal bites, or serious burns, consult a physician.

Directions

clean the affected area at first sign of tingling, burning sensation, or itching.
apply a small amount of this products to the lips and nose prior to exposure to the sun.
in case of cold sore/fever blister indication, apply to area of sensation.
apply up to 4 times a day, and in the evening.
rub in gently.
wash hands before and after applying cream.
do not share product with anyone.
children under 12 years of age: consult a Physician

Uses

for treatment of cold sores/fever blisters on the lips, face, and/or nose

temporarily relieves the symptoms of itching and pain associated with cold sores/fever blisters

prevents outbreak of cold sore/fever blister if applied at first indication of an out break (tingle, or burning sensation)

heals cold sore/fever blisters

prevents and heals sun burn to lips and stimulates rapid healing

Precautions Allergy alert. When using product, Stop and consult Physician,

Warnings

For external use only: Do not use in the eyes, or apply over large areas of the body.

In case of deep or puncture wounds, animal bites, or serious burns, consult a physician.

___________________________________________________________________________________________

Allergy alert: Do not use this product if you are allergic or hypersensitive to any of the ingredients in this product.

___________________________________________________________________________________________

When using this product: Do not get in eyes. Use only as directed.

___________________________________________________________________________________________

Stop using and consult a doctor if the condition persists or gets worse. Do not use longer than 2 weeks unless directed by a doctor.

___________________________________________________________________________________________

Keep out of reach of children. If swallowed, get medical help or contact a Poison Control Center right away at 1-800-222-1222.

INDICATIONS AND USAGE

Do not get in eyes. Use only as directed.